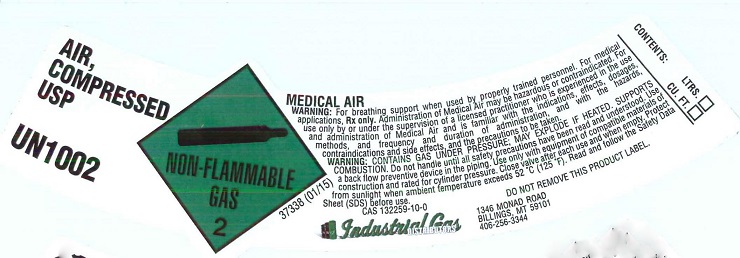 DRUG LABEL: Air
NDC: 55749-017 | Form: GAS
Manufacturer: Industrial Gas Distributors Inc
Category: animal | Type: PRESCRIPTION ANIMAL DRUG LABEL
Date: 20151229

ACTIVE INGREDIENTS: AIR 1000 mL/1 L

Air

PACKAGE LABEL

AIR, COMPRESSED USP UN1002
NON-FLAMMABLE GAS 2
MEDICAL AIR
WARNING: For breathing support when used by properly trained personnel. For medical applications, Rx only. Administration of Medical Air may be hazardous or contraindicated. For use only by or under the supervision of licensed practitioner who is experienced in the use and administration of Medical Air and is familiar with the indications, effects, dosages, methods, and frequency and duration of administration, and with the hazards, contraindications and side effects, and the precautions to be taken.
WARNING: CONTAINS GAS UNDER PRESSURE; MAY EXPLODE IF HEATED. SUPPORTS COMBUSTION. Do not handle until all safety precautions have been read and understood. Use a back flow preventive device in the piping. Use only with equipment of compatible materials of construction and rated for cylinder pressure. Close valve ager each use and when empty. Protect from sunlight when ambient temperature exceeds 52 degrees C (125 degrees F). Read and follow the Safety Data Sheet (SDS) before use.
CAS 132259-10-0 DO NOT REMOVE THIS PRODUCT LABEL
Industrial Gas DISTRIBUTORS 1346 MONAD ROAD BILLINGS, MT 59101 406-256-3344
CONTENTS: LTRS. CU.FT.